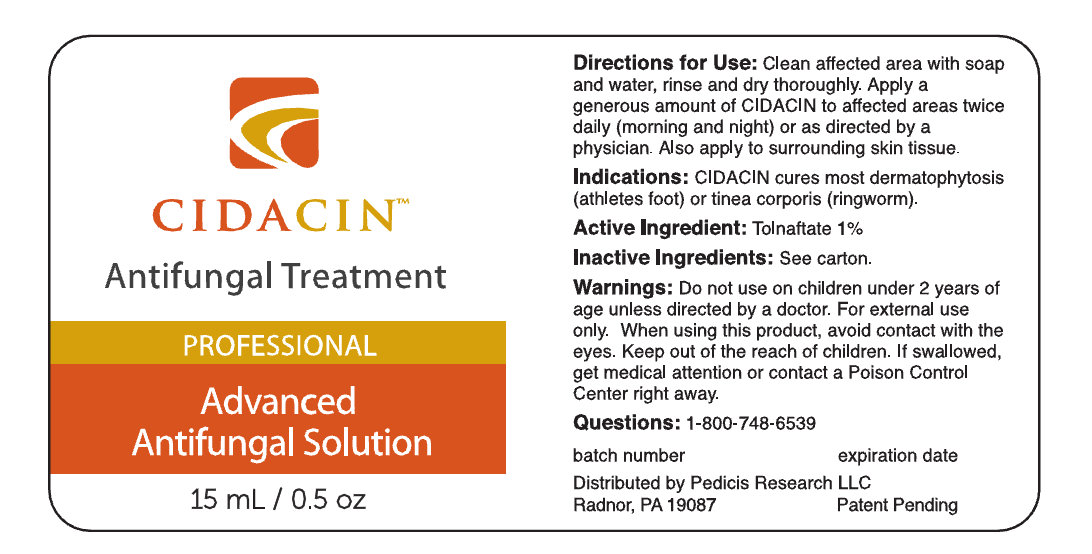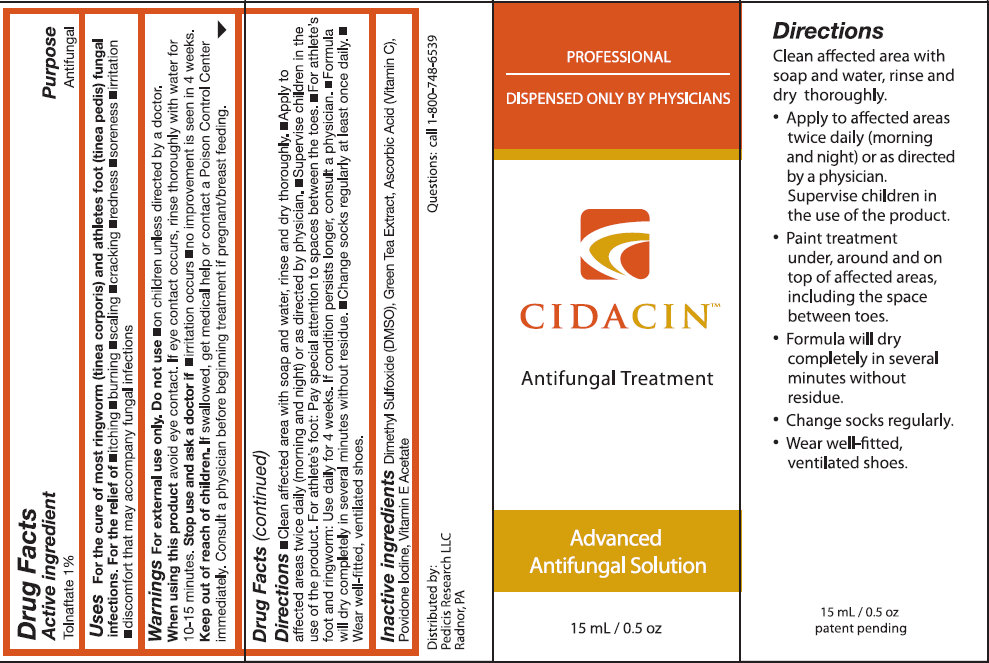 DRUG LABEL: CIDACIN Antifungal Treatment
NDC: 51151-000 | Form: SOLUTION
Manufacturer: Pedicis Research LLC
Category: otc | Type: HUMAN OTC DRUG LABEL
Date: 20231105

ACTIVE INGREDIENTS: TOLNAFTATE 1 g/100 mL
INACTIVE INGREDIENTS: DIMETHYL SULFOXIDE; GREEN TEA LEAF; ASCORBIC ACID; POVIDONE-IODINE; .ALPHA.-TOCOPHEROL ACETATE

CIDACIN Antifungal Treatment

Active Ingredient

Tolnaftate 1%

Purpose

Antifungal

Uses

For the cure of most ringworm (tinea orporis) and athletes foot (tinea pedis) fungal infections. For the relief of itching; burning; scaling; cracking; redness; soreness; irritation; discomfort that may accompany fungal infections.

Warnings

For external use only.

Do not use

on children unless directed by a doctor.

When using this product

avoid eye contact. If eye contact occurs, rinse thoroughly with water for 10-15 minutes.

Stop use and ask a doctor if

- if irritation occurs
- no improvement is seen 4 weeks.

Keep out of reach of children.

If swallowed, get medical help or contact a Poison Control Center immediately.

Consult a physician

before beginning treatment if pregnant/breast feeding.

Directions

- Clean affected area with soap and water, rinse and dry thoroughly.
- Apply to affected areas twice daily (morning and night) or as directed by physician.
- Supervise children in the use of the product.
- For athlete's foot: Pay special attention to spaces between the toes.
- For athlete's foot and ringworm: Use daily for 4 weeks. If condition persists longer, consult physician.
- Formula will dry completely in several minutes without residue.
- Change socks regularly at least once a daily.
- Wear well-fitted, ventilated shoes.

Inactive ingredients

Dimethyl Sulfoxide (DMSO), Green Tea Extract, Ascorbic Acid (Vitamin C), Povidone Iodine, Vitamin E Acetate

Questions:

call 1-800-748-6539

PACKAGE LABEL

PROFESSIONAL DISPENSED ONLY BY PHYSICIANS CIDACIN Antifungal Treatment PROFESSIONAL Advanced Antifungal Solution 15mL / 0.5 oz Distributed by Pedicis Research LLC Radnor, PA 19087 Patent Pending